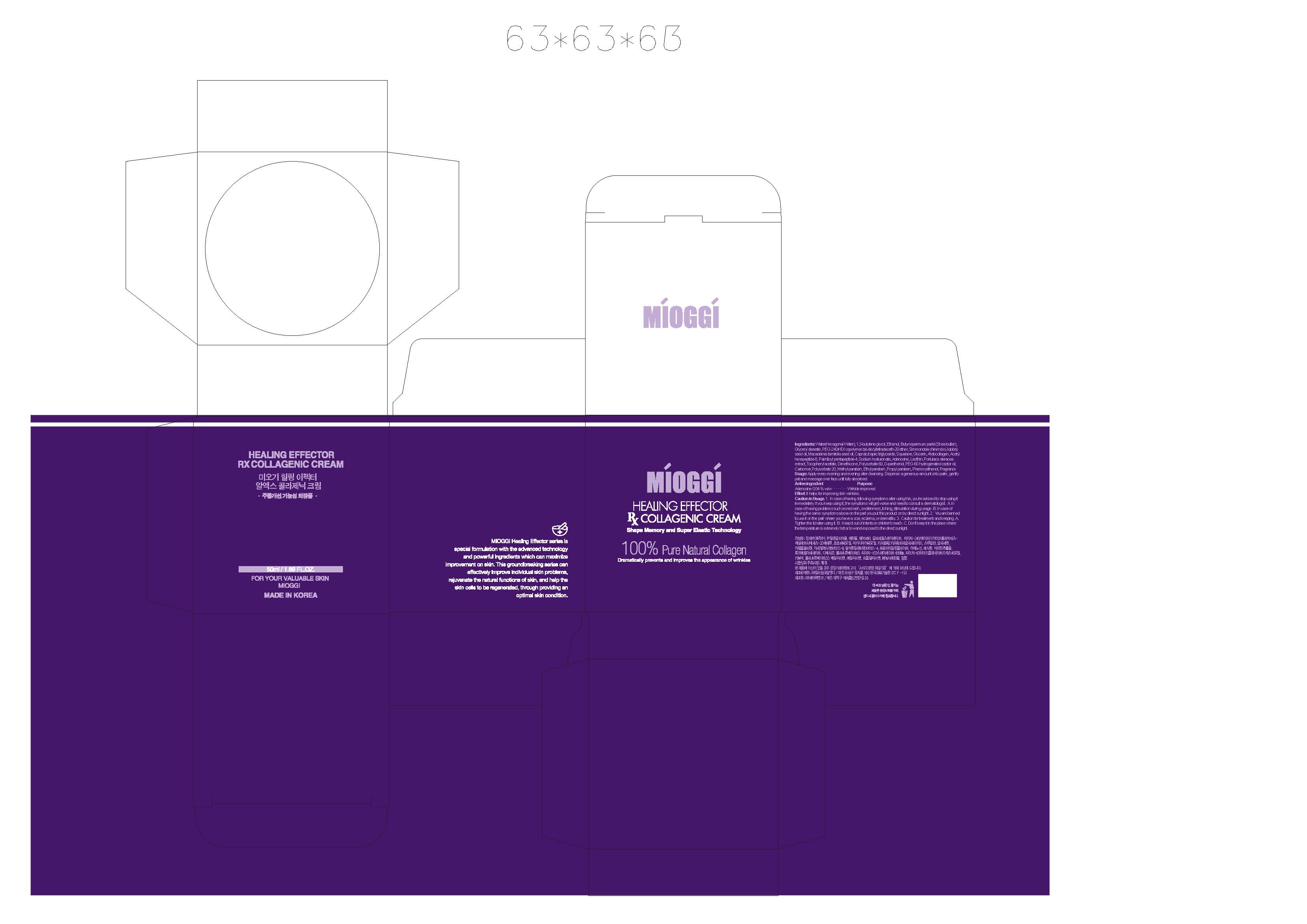 DRUG LABEL: MIOGGI Healing Effector RX Collagenic
                
NDC: 53009-1001 | Form: CREAM
Manufacturer: Colorpink R&D Inc.
Category: otc | Type: HUMAN OTC DRUG LABEL
Date: 20120820

ACTIVE INGREDIENTS: ADENOSINE 0.02 mg/50 mL
INACTIVE INGREDIENTS: SHEA BUTTER; GLYCERYL MONOSTEARATE; POLYETHYLENE GLYCOL 11000; SIMMONDSIA CHINENSIS SEED; MACADAMIA NUT; MEDIUM-CHAIN TRIGLYCERIDES; SQUALANE; GLYCERIN; ACETYL HEXAPEPTIDE-8; PALMITOYL PENTAPEPTIDE-4; HYALURONATE SODIUM; BUTYLENE GLYCOL; LECITHIN, SOYBEAN; PORTULACA OLERACEA WHOLE; .ALPHA.-TOCOPHEROL ACETATE; DIMETHICONE; POLYSORBATE 60; DEXPANTHENOL; POLYOXYL 60 HYDROGENATED CASTOR OIL; POLYSORBATE 20; METHYLPARABEN; ETHYLPARABEN; PROPYLPARABEN; PHENOXYETHANOL

Drug Facts

ACTIVE INGREDIENT

ADENOSINE

INACTIVE INGREDIENT

Water, Butylene glycol, Ethanol, Butyrospermum parkii (Shea Butter), Glyceryl stearate, PEG-240/HDI copolymer bis-decyltetradeceth-20 ether, Simmondsia chinensis (Jojoba) seed oil, Macadamia ternifolia seed oil, Caprylic/capric triglyceride, Squalane, Glycerin, Atelocollagen, Acetyl hexapeptide-8, Palmitoyl pentapeptide-4, Sodium hyaluronate, Adenosine, Lecithin, Portulaca oleracea extract, Tocopheryl acetate, Dimethicone, Polysorbate 60, D-panthenol, PEG-60 hydrogenated castor oil, Carbomer, Polysorbate 20, Methylparaben, Ethylparaben, Proplyparaben, Phenoxyethanol, Fragrance

PURPOSE

for improving skin wrinkles

keep out of reach of the children

INDICATIONS AND USAGE

apply every morning and evening at the end of basic care
gently spread appropriate amount over face using an outer circular motion until fully absorbed

WARNINGS

1. In case of having following symptoms after using this, you're advised to stop using it immediately. If you keep using it, the symptoms will get worse and need to consult a dermatologist.
A. In case of having problems such as red rash, swollenness, itching, stimulation during usage.
B. In case of having the same symptoms above on the part you put this product on by direct sunlight.
2. You are banned to use it on the part where you have a scar, eczema, or dermatitis.
3. Caution for treatment and keeping.
A. Tighten the lid after using it.
B. Keep it out of infants or children's reach.
C. Don't keep it in the place where the temperature is extremely hot or low and exposed to the direct sunlight.

DOSAGE AND ADMINISTRATION

- for external use only